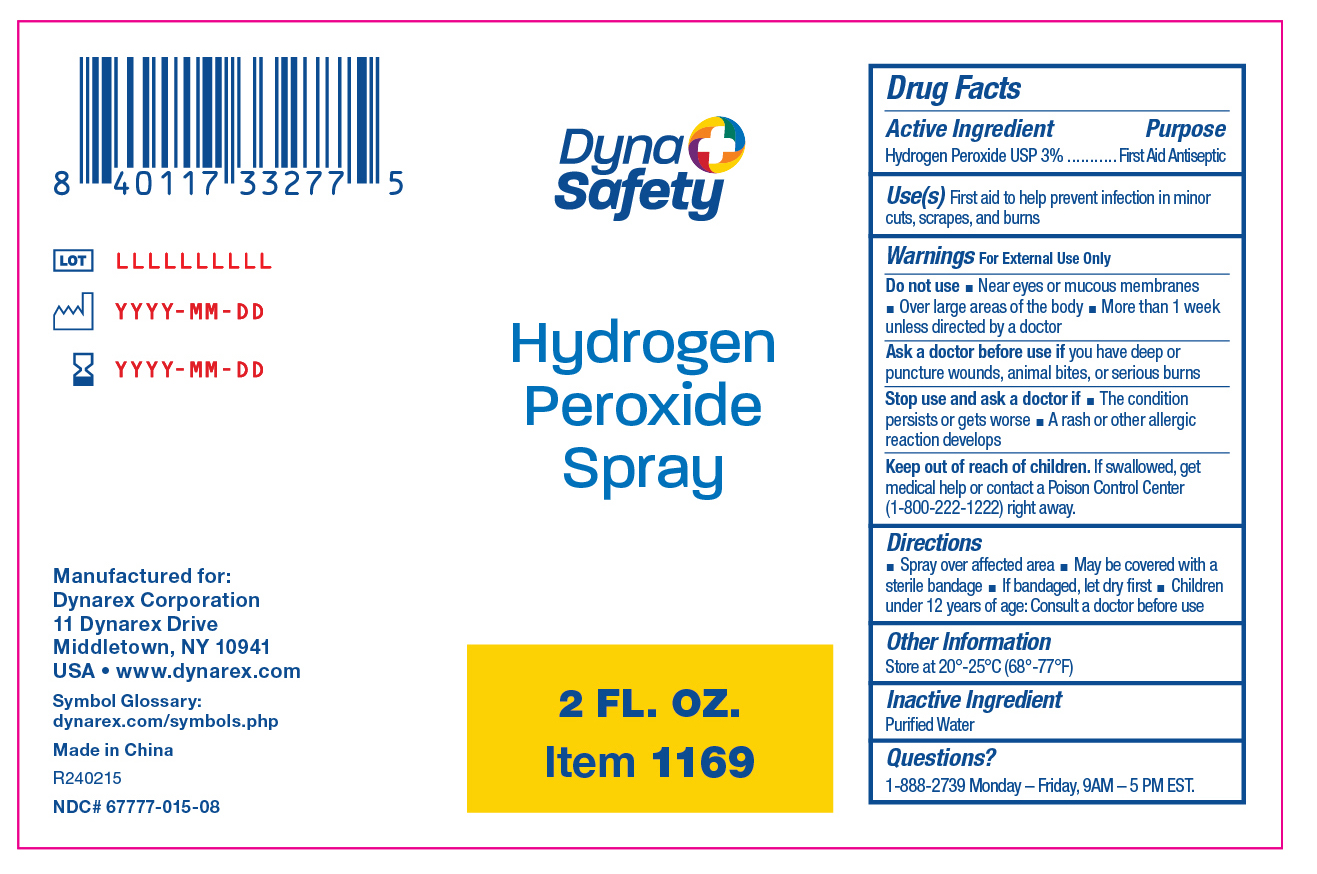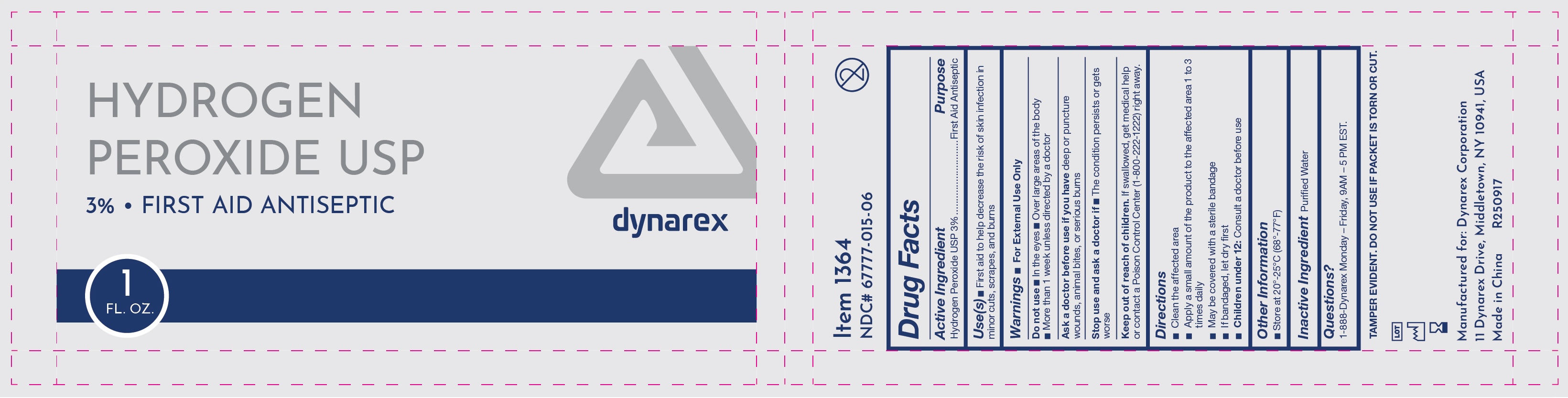 DRUG LABEL: Hydrogen Peroxide
NDC: 67777-015 | Form: SPRAY
Manufacturer: Dynarex Corporation
Category: otc | Type: HUMAN OTC DRUG LABEL
Date: 20251119

ACTIVE INGREDIENTS: HYDROGEN PEROXIDE 0.03 mg/1 mL
INACTIVE INGREDIENTS: WATER

1169 Hydrogen Peroxide Spray
1364 Hydrogen Peroxide Packet

Active ingredient

Hydrogen Peroxide USP 3%

Purpose

First Aid Antiseptic

Uses

• First aid to help decrease the risk of skin infection in minor cuts, scrapes, and burns

Warnings

For External Use Only

Do not use

• In the eyes • Over larege areas of the body • More than 1 week unless directed by a doctor

Ask a doctor before use if

You have deep or puncture wounds, animal bites, or serious burns

Stop use and ask a doctor if

• The condition persists or gets worse

Keep out of reach of children

If swallowed, get medical help or contact a Poison Control Center (1-800-222-1222) right away.

Directions

• Clean the affected area • Apply a small amount of the product to the affected area 1 to 3 times daily • May be covered with a sterile bandage • If bandaged, let dry first

• Children under 12 years of age: Consult a doctor before use

Other information

Store at 20º-25ºC (68º-77ºF)

Inactive ingredient

Purified Water

Questions?

1-888-Dynarex Monday - Friday, 9AM - 5PM EST.

Label

1169 Label

Label

1364